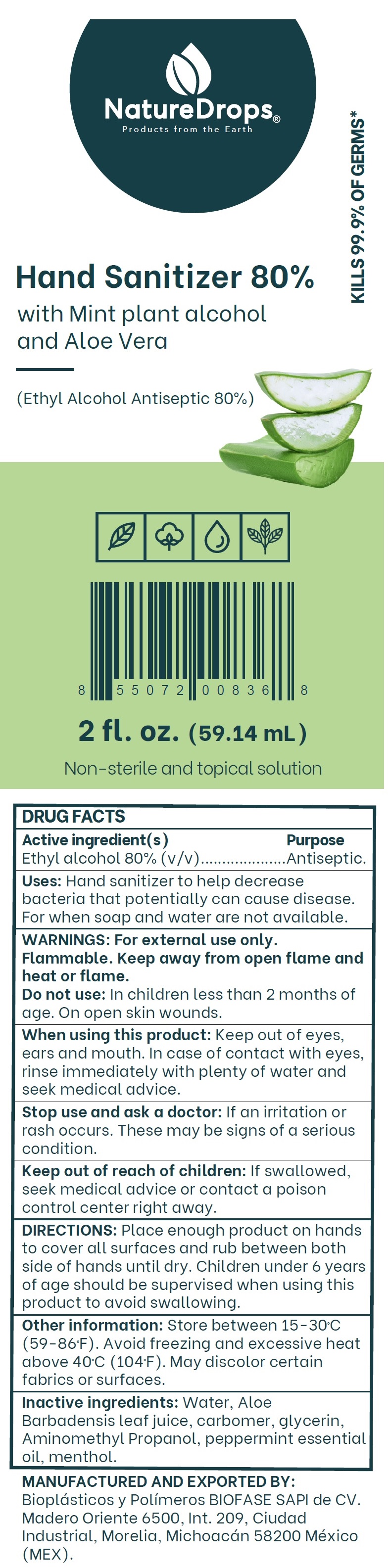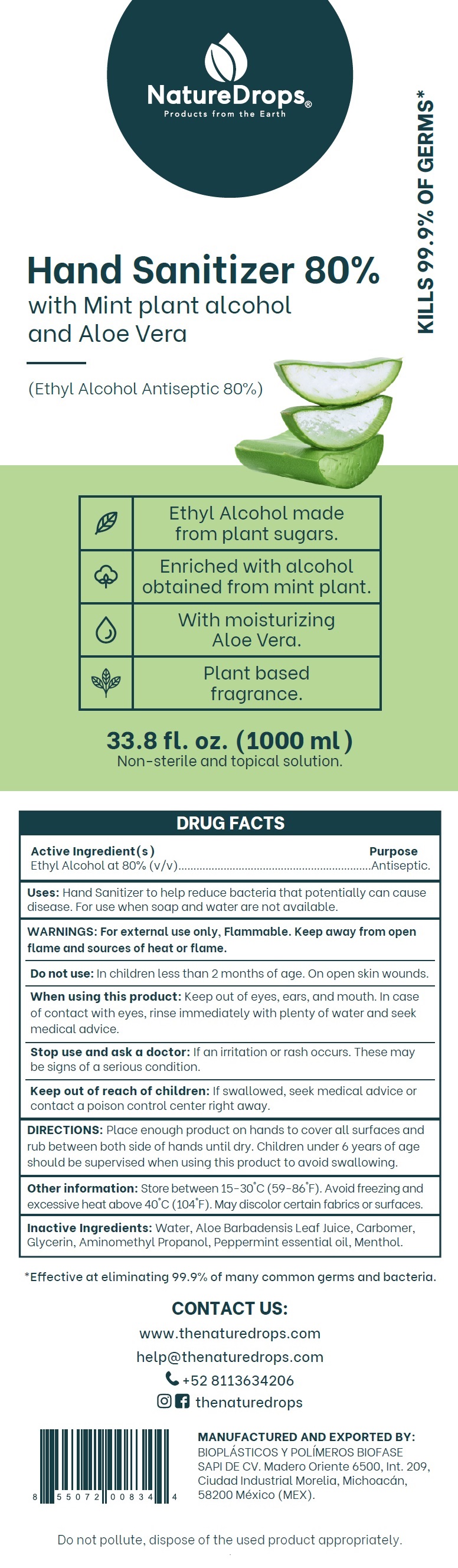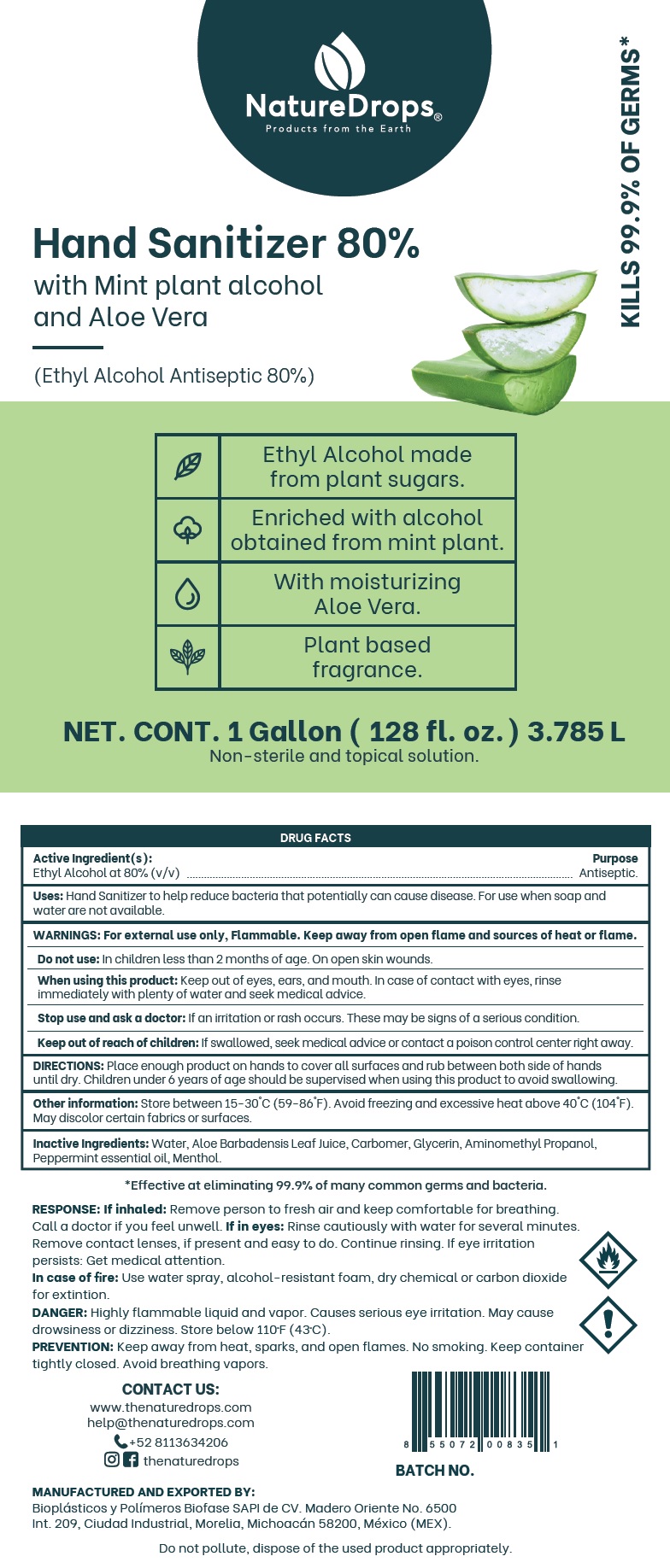 DRUG LABEL: NatureDrops Hand Sanitizer 80%
NDC: 77452-004 | Form: GEL
Manufacturer: Bioplasticos y Polimeros BIOFASE, S.A.P.I. de C.V.
Category: otc | Type: HUMAN OTC DRUG LABEL
Date: 20200922

ACTIVE INGREDIENTS: ALCOHOL 80 mL/100 mL
INACTIVE INGREDIENTS: WATER; ALOE VERA LEAF; CARBOMER HOMOPOLYMER, UNSPECIFIED TYPE; GLYCERIN; AMINOMETHYLPROPANOL; PEPPERMINT OIL; MENTHOL, UNSPECIFIED FORM

NatureDrops® Hand Sanitizer

Active Ingredient(s)

Ethyl Alcohol at 80% (v/v)

Purpose

Antiseptic

INDICATIONS AND USAGE

Uses: Hand Sanitizer to help reduce bacteria that potentially can cause disease. For use when soap and water are not available.

WARNINGS

WARNINGS: For external use only, Flammable. Keep away from open flame and sources of heat or flame.

Do not use: In children less than 2 months of age. On open skin wounds.

When using this product: Keep out of eyes, ears, and mouth. In case of contact with eyes, rinse

immediately with plenty of water and seek medical advice.

Stop use and ask a doctor: If an irritation or rash occurs. These may be signs of a serious condition.

Keep out of reach of children: If swallowed, seek medical advice or contact a poison control center right away.

DOSAGE AND ADMINISTRATION

DIRECTIONS: Place enough product on hands to cover all surfaces and rub between both side of hands until dry. Children under 6 years of age should be supervised when using this product to avoid swallowing.

Other information: Store between 15-30°C (59-86°F). Avoid freezing and excessive heat above 40°C (104°F). May discolor certain fabrics or surfaces.

INACTIVE INGREDIENT

Inactive Ingredients: Water, Aloe Barbadensis Leaf Juice, Carbomer, Glycerin, Aminomethyl Propanol, Peppermint essential oil, Menthol.

Products from the Earth

with Mint plant alcohol and Aloe Vera

KILLS 99.9% OF GERMS*

Ethyl Alcohol made from plant sugars.

Enriched with alcohol obtained from mint plant.

With moisturizing Aloe Vera.

Plant based fragrance.

Non-sterile and topical solution.

*Effective at eliminating 99.9% of many common germs and bacteria.

RESPONSE: If inhaled: Remove person to fresh air and keep comfortable for breathing.

Call a doctor if you feel unwell. If in eyes: Rinse cautiously with water for several minutes.

Remove contact lenses, if present and easy to do. Continue rinsing. If eye irritation persists: Get medical attention.

In case of fire: Use water spray, alcohol-resistant foam, dry chemical or carbon dioxide for extintion.

DANGER: Highly flammable liquid and vapor. Causes serious eye irritation. May cause drowsiness or dizziness. Store below 110ºF (43ºC).

PREVENTION: Keep away from heat, sparks, and open flames. No smoking. Keep container tightly closed. Avoid breathing vapors.

CONTACT US:

www.thenaturedrops.com

help@thenaturedrops.com

+52 8113634206

thenaturedrops

MANUFACTURED AND EXPORTED BY:

Bioplásticos y Polímeros Biofase SAPI de CV. Madero Oriente No. 6500

Int. 209, Ciudad Industrial, Morelia, Michoacán 58200, México (MEX).

Do not pollute, dispose of the used product appropriately.